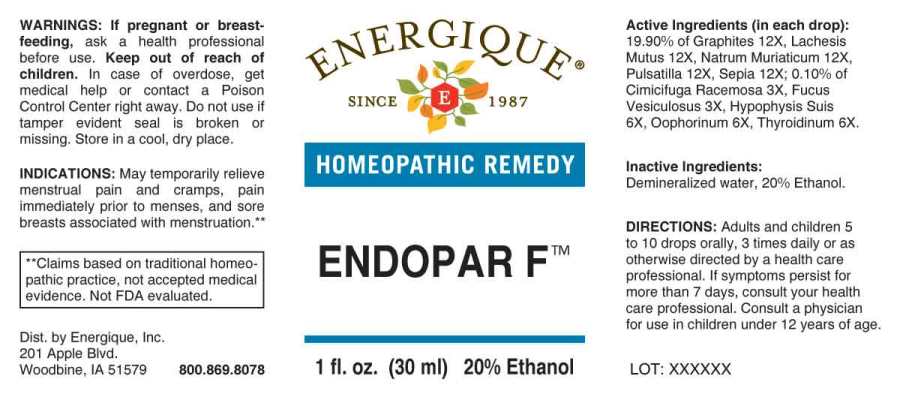 DRUG LABEL: Endopar
NDC: 44911-0308 | Form: LIQUID
Manufacturer: Energique, Inc.
Category: homeopathic | Type: HUMAN OTC DRUG LABEL
Date: 20230607

ACTIVE INGREDIENTS: BLACK COHOSH 3 [hp_X]/1 mL; FUCUS VESICULOSUS 3 [hp_X]/1 mL; SUS SCROFA OVARY 6 [hp_X]/1 mL; SUS SCROFA PITUITARY GLAND 6 [hp_X]/1 mL; THYROID 6 [hp_X]/1 mL; GRAPHITE 12 [hp_X]/1 mL; LACHESIS MUTA VENOM 12 [hp_X]/1 mL; SODIUM CHLORIDE 12 [hp_X]/1 mL; PULSATILLA PRATENSIS WHOLE 12 [hp_X]/1 mL; SEPIA OFFICINALIS JUICE 12 [hp_X]/1 mL
INACTIVE INGREDIENTS: WATER; ALCOHOL

Drug Facts:

ACTIVE INGREDIENTS:

(in each drop): 19.90% of Graphites 12X, Lachesis Mutus 12X, Natrum Muriaticum 12X, Pulsatilla (Pratensis) 12X, Sepia 12X; 0.10% of Cimicifuga Racemosa 3X, Fucus Vesiculosus 3X, , Hypophysis Suis 6X, Oophorinum (Suis) 6X, Thyroidinum (Suis) 6X.

INDICATIONS:

May temporarily relieve menstrual pain and cramps, pain immediately prior to menses, and sore breasts associated with menstruation.**

**Claims based on traditional homeopathic practice, not accepted medical evidence. Not FDA evaluated.

WARNINGS:

If pregnant or breast-feeding, ask a health professional before use.

Keep out of reach of children. In case of overdose, get medical help or contact a Poison Control Center right away.

Do not use if tamper evident seal is broken or missing. Store in a cool, dry place.

Keep out of reach of children. In case of overdose, get medical help or contact a Poison Control Center right away.

DIRECTIONS:

Adults and children 5 to 10 drops orally, 3 times daily or as otherwise directed by a health care professional. If symptoms persist for more than 7 days, consult your health care professional. Consult a physician for use in children under 12 years of age.

INDICATIONS:

May temporarily relieve menstrual pain and cramps, pain immediately prior to menses, and sore breasts associated with menstruation.**

**Claims based on traditional homeopathic practice, not accepted medical evidence. Not FDA evaluated.

INACTIVE INGREDIENTS:

Demineralized water, 20% Ethanol.

QUESTIONS:

Dist. by Energique, Inc.

201 Apple Blvd.

Woodbine, IA 51579 800.869.8078

PACKAGE LABEL DISPLAY:

ENERGIQUE
SINCE 1987
HOMEOPATHIC REMEDY
ENDOPAR F
1 fl. oz. (30 ml)